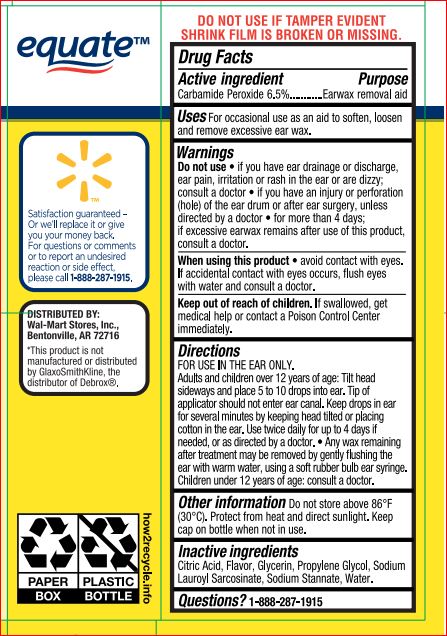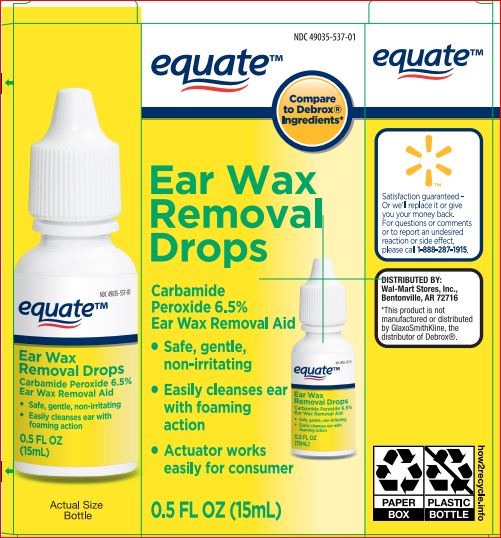 DRUG LABEL: Earwax Removal Drops

NDC: 49035-537 | Form: LIQUID
Manufacturer: Walmart
Category: otc | Type: HUMAN OTC DRUG LABEL
Date: 20171229

ACTIVE INGREDIENTS: CARBAMIDE PEROXIDE 6.5 g/100 mL
INACTIVE INGREDIENTS: ANHYDROUS CITRIC ACID; GLYCERIN; PROPYLENE GLYCOL; SODIUM LAUROYL SARCOSINATE; SODIUM STANNATE; WATER

Drug Facts 25-119PQ

Active ingredient Purpose

Carbamide peroxide 6.5% Earwax removal aid

INDICATIONS AND USAGE

For occasional use as an aid to soften, loosen and remove excessive earwax

Warnings

Do not use • if you have ear drainage or discharge,
ear pain, irritation or rash in the ear or are dizzy;
consult a doctor • if you have an injury or perforation
(hole) of the ear drum or after ear surgery, unless
directed by a doctor • for more than 4 consecutive
days; if excessive earwax remains after use of this
product, consult a doctor

When using this product • avoid contact with eyes.
If accidental contact with eyes occurs, flush eyes
with water and consult a doctor

Keep out of reach of the children
If product is swallowed, get medical help or contact a Poison Control Center right away

Directions

FOR USE IN THE EAR ONLY.
Adults and children over 12 years of age: Tilt head
sideways and place 5 to 10 drops into ear. Tip of
applicator should not enter ear canal. Keep drops in
ear for several minutes by keeping head tilted or
placing cotton in the ear. Use twice daily for up to 4
days if needed, or as directed by a doctor. • Any wax
remaining after the 4-day treatment may be removed
by gently flushing the ear with warm water, using a
soft rubber bulb ear syringe.
Children under 12 years of age: consult a doctor

INACTIVE INGREDIENT

Citric Acid, Flavor, Glycerin, Propylene Glycol, Sodium Lauroyl Sarcosinate, Sodium Stannate, Water